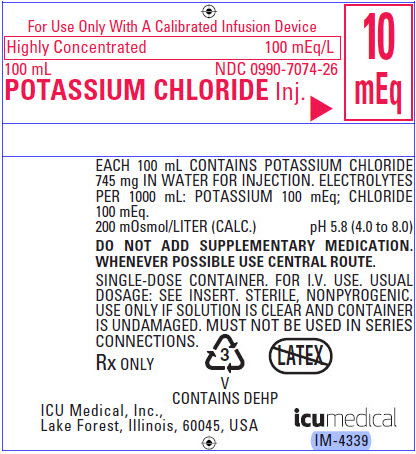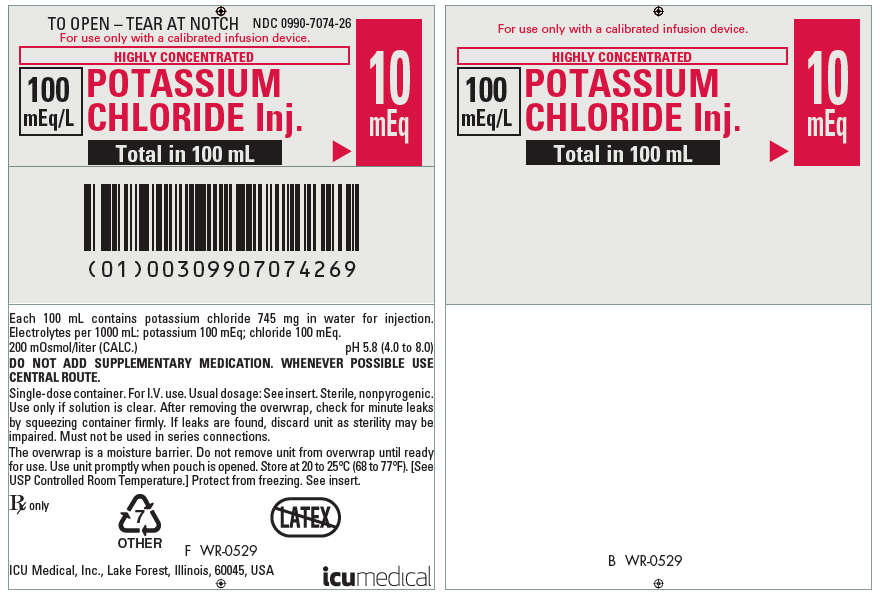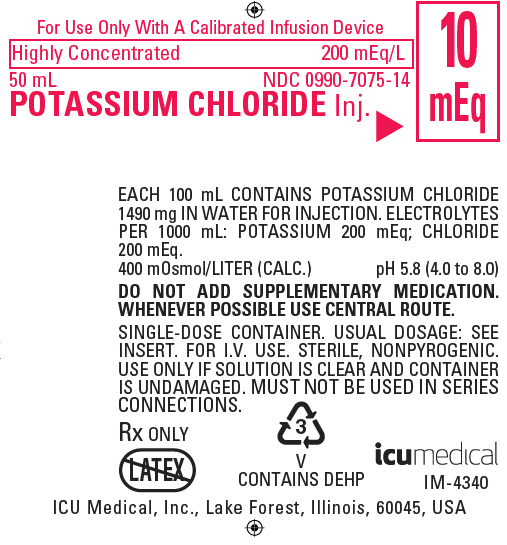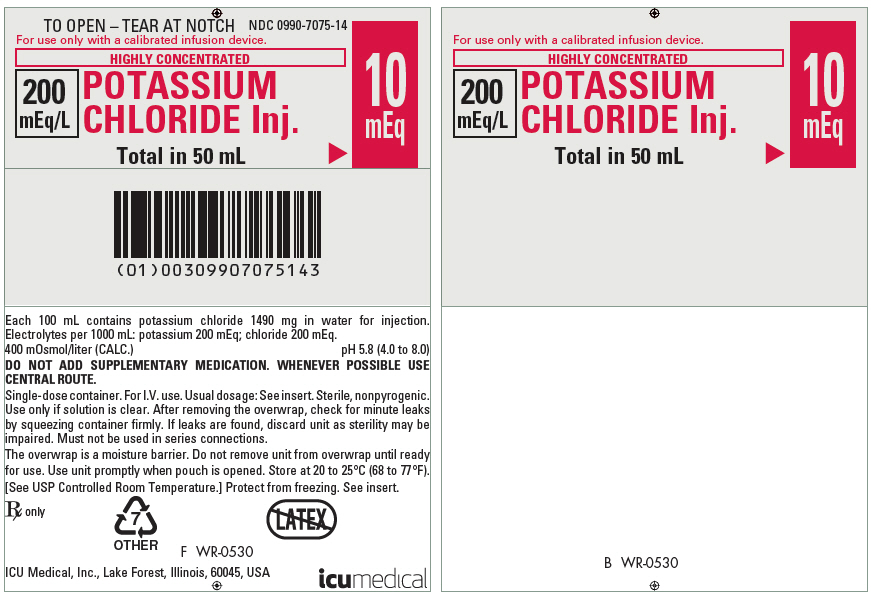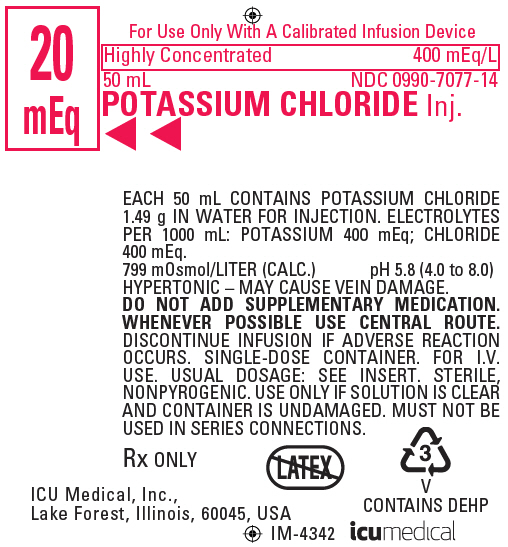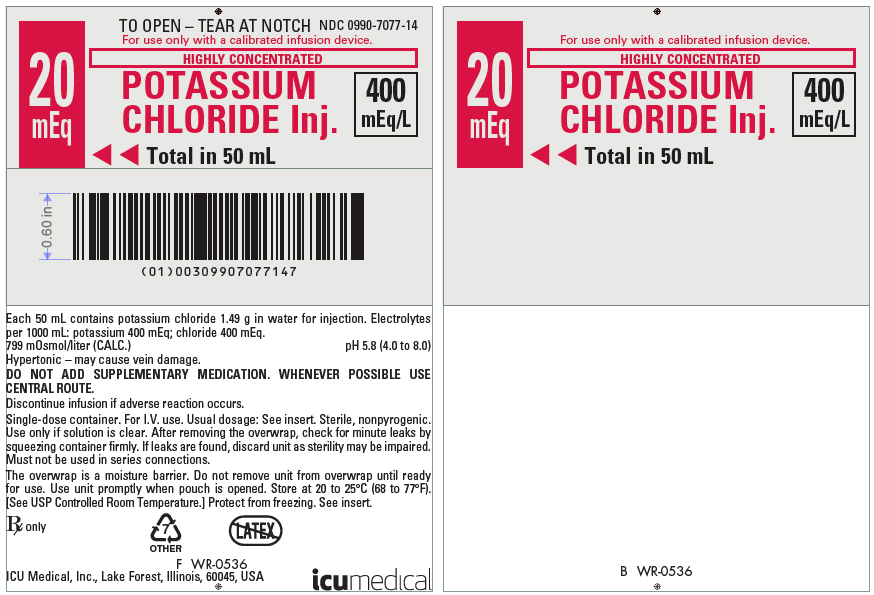 DRUG LABEL: Potassium Chloride
NDC: 0990-7074 | Form: INJECTION, SOLUTION
Manufacturer: ICU Medical Inc.
Category: prescription | Type: HUMAN PRESCRIPTION DRUG LABEL
Date: 20251029

ACTIVE INGREDIENTS: POTASSIUM CHLORIDE 10 meq/100 mL
INACTIVE INGREDIENTS: WATER

POTASSIUM CHLORIDE INJECTION

For Use Only With A Calibrated Infusion Device

BOXED WARNING

Highly Concentrated

Flexible Plastic Container

Ready To Use

Rx only

DESCRIPTION

This Potassium Chloride Injection is a sterile, nonpyrogenic, highly concentrated, ready-to-use solution of Potassium Chloride, USP in Water for Injection, USP for electrolyte replenishment in a single dose container for intravenous administration. It contains no antimicrobial agents.

Potassium; Chloride; Injection; mEq Potassium/; Container | Composition; (g/L); Potassium; Chloride, USP; (KCl) | Osmolarity*; (mOsmol/L); (calc) | pH | Ionic Concentration; (mEq/L)
Potassium; Chloride; Injection; mEq Potassium/; Container | Composition; (g/L); Potassium; Chloride, USP; (KCl) | Osmolarity*; (mOsmol/L); (calc) | pH | Potassium | Chloride
10 mEq/100 mL | 7.45 | 200 | 5.8; (4.0 to 8.0) | 100 | 100
10 mEq/50 mL; 20 mEq/100 mL | 14.9 | 400 | 5.8; (4.0 to 8.0) | 200 | 200
20 mEq/50 mL; 40 mEq/100 mL | 29.8 | 799 | 5.8; (4.0 to 8.0) | 400 | 400

*Normal physiologic osmolarity range is approximately 280 to 310 mOsmol/L. Administration of substantially hypertonic solutions (≥600 mOsmol/L) may cause vein damage.

This flexible plastic container is fabricated from a specially formulated polyvinylchloride. Exposure to temperatures above 25°C (77°F) during transport and storage will lead to minor losses in moisture content. Higher temperatures lead to greater losses. It is unlikely that these minor losses will lead to clinically significant changes within the expiration period. The amount of water that can permeate from inside the container into the overwrap is insufficient to affect the solution significantly. Solutions in contact with the plastic container may leach out certain of its chemical components from the plastic in very small amounts; however, biological testing was supportive of the safety of the plastic container materials.

CLINICAL PHARMACOLOGY

Potassium is the major cation of body cells (160 mEq/liter of intracellular water) and is concerned with the maintenance of body fluid composition and electrolyte balance. Potassium participates in carbohydrate utilization, protein synthesis, and is critical in the regulation of nerve conduction and muscle contraction, particularly in the heart. Chloride, the major extracellular anion, closely follows the metabolism of sodium, and changes in the acid-base of the body are reflected by changes in the chloride concentration.

Normally about 80 to 90% of the potassium intake is excreted in the urine, the remainder in the stools and to a small extent, in the perspiration. The kidney does not conserve potassium well so that during fasting, or in patients on a potassium-free diet, potassium loss from the body continues resulting in potassium depletion. A deficiency of either potassium or chloride will lead to a deficit of the other.

INDICATIONS AND USAGE

Potassium Chloride Injection is indicated in the treatment of potassium deficiency states when oral replacement is not feasible.

THIS HIGHLY CONCENTRATED, READY-TO-USE POTASSIUM CHLORIDE INJECTION IS INTENDED FOR THE MAINTENANCE OF SERUM K ^+ LEVELS AND FOR POTASSIUM SUPPLEMENTATION IN FLUID RESTRICTED PATIENTS WHO CANNOT ACCOMMODATE ADDITIONAL VOLUMES OF FLUID ASSOCIATED WITH POTASSIUM SOLUTIONS OF LOWER CONCENTRATION.

When using these products, these patients should be on continuous cardiac monitoring and frequent testing for serum potassium concentration and acid-base balance.

CONTRAINDICATIONS

Potassium Chloride Injection is contraindicated in diseases where high potassium levels may be encountered, and in patients with hyperkalemia, renal failure and in conditions in which potassium retention is present.

WARNINGS

THIS HIGHLY CONCENTRATED, READY-TO-USE POTASSIUM CHLORIDE INJECTION IS INTENDED FOR THE MAINTENANCE OF SERUM K ^+ LEVELS AND FOR POTASSIUM SUPPLEMENTATION IN FLUID RESTRICTED PATIENTS WHO CANNOT ACCOMMODATE ADDITIONAL VOLUMES OF FLUID ASSOCIATED WITH POTASSIUM SOLUTIONS OF LOWER CONCENTRATION.

TO AVOID POTASSIUM INTOXICATION, DO NOT INFUSE THESE SOLUTIONS RAPIDLY.

PATIENTS REQUIRING HIGHLY CONCENTRATED SOLUTIONS SHOULD BE KEPT ON CONTINUOUS CARDIAC MONITORING AND UNDERGO FREQUENT TESTING FOR SERUM POTASSIUM AND ACID-BASE BALANCE, ESPECIALLY IF THEY RECEIVE DIGITALIS.

In patients with renal insufficiency, administration of potassium chloride may cause potassium intoxication and life-threatening hyperkalemia.

Administer intravenously only with a calibrated infusion device at a slow, controlled rate. (See DOSAGE AND ADMINISTRATION.) Because pain associated with peripheral infusion of Potassium Chloride solution has been reported, whenever possible administration via a central route is recommended for thorough dilution by the blood stream and avoidance of extravasation. Highest concentrations (300 and 400 mEq/L) should be exclusively administered via central route.

The administration of intravenous solutions can cause fluid and/or solute overload resulting in dilution of serum electrolyte concentrations, overhydration, congested states or pulmonary edema. The risk of dilutional states is inversely proportional to the electrolyte concentration. The risk of solute overload causing congested states with peripheral and pulmonary edema is directly proportional to the electrolyte concentration.

PRECAUTIONS

Laboratory Tests

Serum potassium levels are not necessarily indicative of tissue potassium levels. Solutions containing potassium should be used with caution in the presence of cardiac or renal disease.

Clinical evaluation and periodic laboratory determinations are necessary to monitor changes in fluid balance, electrolyte concentrations, and acid-base balance during prolonged parenteral therapy or whenever the condition of the patient warrants such evaluation. Significant deviations from normal concentrations may require the use of additional electrolyte supplements, or the use of electrolyte-free dextrose solutions to which individualized electrolyte supplements may be added.

Pregnancy:

Pregnancy Category C. Animal reproduction studies have not been conducted with potassium chloride. It is also not known whether potassium chloride can cause fetal harm when administered to a pregnant woman or can affect reproduction capacity. Potassium chloride should be given to a pregnant woman only if clearly needed.

Pediatric Use:

These products should not be used in pediatric patients at this time.

Do not administer unless solution is clear and seal is intact.

ADVERSE REACTIONS

Potassium intoxication with mild or severe hyperkalemia has been reported. The signs and symptoms of intoxication include paresthesia of the extremities, areflexia, muscular or respiratory paralysis, mental confusion, weakness, hypotension, cardiac arrhythmia, heart block, electrographic abnormalities and cardiac arrest. EKG abnormalities serve as a clinical reflection of the seriousness of changes in serum potassium concentrations: peaked T waves and prolonged P-R intervals usually occur with modest elevations above the upper limit of normal potassium concentrations; P waves disappear, the QRS complex widens, and eventual asystole usually occurs with higher elevations.

Reactions which may occur because of the solution or the technique of administration include febrile response, infection at the site of injection, venous thrombosis or phlebitis extending from the site of injection, extravasation and hypervolemia.

Infusion of highly concentrated potassium chloride solutions may cause local pain and vein irritation. (See WARNINGS).

Reactions reported with the use of potassium-containing solutions include nausea, vomiting, and abdominal pain and diarrhea.

If an adverse reaction does occur, discontinue the infusion, evaluate the patient, institute appropriate therapeutic countermeasures and save the remainder of the fluid for examination if deemed necessary.

OVERDOSAGE

In the event of hyperkalemia, discontinue the infusion immediately and institute corrective therapy to reduce serum potassium levels as necessary. The use of potassium containing foods or medications must also be eliminated.

Treatment of mild to severe hyperkalemia with signs and symptoms of potassium intoxication includes the following:

1. Dextrose Injection, USP, 10% or 25%, containing 10 units of crystalline insulin per 20 grams of dextrose administered intravenously, 300 to 500 mL per hour.
2. Absorption and exchange of potassium using sodium or ammonium cycle cation exchange resin, orally and as retention enema.
3. Hemodialysis and peritoneal dialysis.

In cases of digitalization, too rapid a lowering of plasma potassium concentration can cause digitalis toxicity.

DOSAGE AND ADMINISTRATION

The dose and rate of administration are dependent upon the specific condition of each patient.

Administer intravenously only with a calibrated infusion device at a slow, controlled rate. Because pain associated with peripheral infusion of Potassium Chloride solution has been reported, whenever possible, administration via central route is recommended for thorough dilution by the blood stream and avoidance of extravasation. Highest concentrations (300 and 400 mEq/L) should be exclusively administered via central route.

Recommended administration rates should not usually exceed 10 mEq/hour or 200 mEq for a 24-hour period if the serum potassium level is greater than 2.5 mEq/liter.

In urgent cases where the serum potassium level is less than 2 mEq/liter or where severe hypokalemia is a threat (serum potassium level less than 2 mEq/liter and electrocardiographic changes and/or muscle paralysis), rates up to 40 mEq/hour or 400 mEq over a 24-hour period can be administered very carefully when guided by continuous monitoring of the EKG and frequent serum K^+ determinations to avoid hyperkalemia and cardiac arrest.

Parenteral drug products should be inspected visually for particulate matter and discoloration, whenever solution and container permit. Use of a final filter is recommended during administration of all parenteral solutions where possible.

Do not add supplementary medication.

Preparation for Administration

(Use aseptic technique)

1. Close flow control clamp of administration set.
2. Remove cover from outlet port at bottom of container.
3. Insert piercing pin of administration set into port with a twisting motion until the set is firmly seated. NOTE: See full directions on administration set carton.
4. Suspend container from hanger.
5. Squeeze and release drip chamber to establish proper fluid level in chamber.
6. Open flow control clamp and clear air from set. Close clamp.
7. Attach set to venipuncture device. If device is not indwelling, prime and make venipuncture.
8. Regulate rate of administration with flow control clamp.

WARNING: Do not use flexible container in series connections. Do not add supplementary medication. Such use could result in air embolism due to residual air being drawn from the primary container before administration of the fluid from the secondary container is completed.

HOW SUPPLIED

Potassium Chloride Injection in flexible plastic containers is available as follows:

NDC No. | Potassium per container
0409–7074–26 | 10 mEq/100 mL
0990-7074-26 | 10 mEq/100 mL
0409–7075–14 | 10 mEq/50 mL
0990-7075-14 | 10 mEq/50 mL
0409–7075–26 | 20 mEq/100 mL
0990-7075-26 | 20 mEq/100 mL
0409–7077–14 | 20 mEq/50 mL
0990-7077-14 | 20 mEq/50 mL
0409–7077–26 | 40 mEq/100 mL
0990-7077-26 | 40 mEq/100 mL

ICU Medical is transitioning NDC codes from "0409" to a "0990" labeler code. Both NDC codes are expected to be in the market for a period of time.

Store at 20 to 25°C (68 to 77°F). [See USP Controlled Room Temperature.]

Revised: June, 2018 | EN-4654

ICU Medical, Inc., Lake Forest, Illinois, 60045, USA

PRINCIPAL DISPLAY PANEL - 100 mL Bag Label

For Use Only With A Calibrated Infusion Device

Highly Concentrated
100 mEq/L

100 mL
NDC 0990-7074-26

POTASSIUM CHLORIDE Inj.

10
mEq

EACH 100 mL CONTAINS POTASSIUM CHLORIDE
745 mg IN WATER FOR INJECTION. ELECTROLYTES
PER 1000 mL: POTASSIUM 100 mEq; CHLORIDE
100 mEq.
200 mOsmol/LITER (CALC.)
pH 5.8 (4.0 to 8.0)

DO NOT ADD SUPPLEMENTARY MEDICATION.
WHENEVER POSSIBLE USE CENTRAL ROUTE.

SINGLE-DOSE CONTAINER. FOR I.V. USE. USUAL
DOSAGE: SEE INSERT. STERILE, NONPYROGENIC.
USE ONLY IF SOLUTION IS CLEAR AND CONTAINER
IS UNDAMAGED. MUST NOT BE USED IN SERIES
CONNECTIONS.

Rx ONLY

3
V
CONTAINS DEHP

ICU Medical, Inc.,
Lake Forest, Illinois, 60045, USA

icumedical

IM-4339

PRINCIPAL DISPLAY PANEL - 100 mL Bag Pouch Label

TO OPEN – TEAR AT NOTCH
NDC 0990-7074-26
For use only with a calibrated infusion device.
HIGHLY CONCENTRATED

100
mEq/L

POTASSIUM
CHLORIDE Inj.

10
mEq

Total in 100 mL

Each 100 mL contains potassium chloride 745 mg in water for injection.
Electrolytes per 1000 mL: potassium 100 mEq; chloride 100 mEq.
200 mOsmol/liter (CALC.)
pH 5.8 (4.0 to 8.0)

DO NOT ADD SUPPLEMENTARY MEDICATION. WHENEVER POSSIBLE USE
CENTRAL ROUTE.

Single-dose container. For I.V. use. Usual dosage: See insert. Sterile, nonpyrogenic.
Use only if solution is clear. After removing the overwrap, check for minute leaks
by squeezing container firmly. If leaks are found, discard unit as sterility may be
impaired. Must not be used in series connections.

The overwrap is a moisture barrier. Do not remove unit from overwrap until ready
for use. Use unit promptly when pouch is opened. Store at 20 to 25°C (68 to 77°F). [See
USP Controlled Room Temperature.] Protect from freezing. See insert.

Rx only

7
OTHER

F WR-0529

ICU Medical, Inc., Lake Forest, Illinois, 60045, USA

icumedical

PRINCIPAL DISPLAY PANEL - 50 mL Bag Label - IM-4340

For Use Only With A Calibrated Infusion Device

Highly Concentrated
200 mEq/L

50 mL
NDC 0990-7075-14

POTASSIUM CHLORIDE Inj.

10
mEq

EACH 100 mL CONTAINS POTASSIUM CHLORIDE
1490 mg IN WATER FOR INJECTION. ELECTROLYTES
PER 1000 mL: POTASSIUM 200 mEq; CHLORIDE
200 mEq.
400 mOsmol/LITER (CALC.)
pH 5.8 (4.0 to 8.0)

DO NOT ADD SUPPLEMENTARY MEDICATION.
WHENEVER POSSIBLE USE CENTRAL ROUTE.

SINGLE-DOSE CONTAINER. USUAL DOSAGE: SEE
INSERT. FOR I.V. USE. STERILE, NONPYROGENIC.
USE ONLY IF SOLUTION IS CLEAR AND CONTAINER
IS UNDAMAGED. MUST NOT BE USED IN SERIES
CONNECTIONS.

Rx ONLY

3
V
CONTAINS DEHP

icumedical

IM-4340

ICU Medical, Inc., Lake Forest, Illinois, 60045, USA

PRINCIPAL DISPLAY PANEL - 50 mL Bag Pouch Label - WR-0530

TO OPEN – TEAR AT NOTCH
NDC 0990-7075-14
For use only with a calibrated infusion device.
HIGHLY CONCENTRATED

200
mEq/L

POTASSIUM
CHLORIDE Inj.

10
mEq

Total in 50 mL

Each 100 mL contains potassium chloride 1490 mg in water for injection.
Electrolytes per 1000 mL: potassium 200 mEq; chloride 200 mEq.
400 mOsmol/liter (CALC.)
pH 5.8 (4.0 to 8.0)

DO NOT ADD SUPPLEMENTARY MEDICATION. WHENEVER POSSIBLE USE
CENTRAL ROUTE.

Single-dose container. For I.V. use. Usual dosage: See insert. Sterile, nonpyrogenic.
Use only if solution is clear. After removing the overwrap, check for minute leaks
by squeezing container firmly. If leaks are found, discard unit as sterility may be
impaired. Must not be used in series connections.

The overwrap is a moisture barrier. Do not remove unit from overwrap until ready
for use. Use unit promptly when pouch is opened. Store at 20 to 25°C (68 to 77°F).
[See USP Controlled Room Temperature.] Protect from freezing. See insert.

Rx only

7
OTHER

F WR-0530

ICU Medical, Inc., Lake Forest, Illinois, 60045, USA

icumedical

PRINCIPAL DISPLAY PANEL - 50 mL Bag Label - IM-4342

For Use Only With A Calibrated Infusion Device

Highly Concentrated
400 mEq/L

50 mL
NDC 0990-7077-14

POTASSIUM CHLORIDE Inj.

20
mEq

EACH 50 mL CONTAINS POTASSIUM CHLORIDE
1.49 g IN WATER FOR INJECTION. ELECTROLYTES
PER 1000 mL: POTASSIUM 400 mEq; CHLORIDE
400 mEq.
799 mOsmol/LITER (CALC.)
pH 5.8 (4.0 to 8.0)
HYPERTONIC – MAY CAUSE VEIN DAMAGE.
DO NOT ADD SUPPLEMENTARY MEDICATION.
WHENEVER POSSIBLE USE CENTRAL ROUTE.
DISCONTINUE INFUSION IF ADVERSE REACTION
OCCURS. SINGLE-DOSE CONTAINER. FOR I.V.
USE. USUAL DOSAGE: SEE INSERT. STERILE,
NONPYROGENIC. USE ONLY IF SOLUTION IS CLEAR
AND CONTAINER IS UNDAMAGED. MUST NOT BE
USED IN SERIES CONNECTIONS.

Rx ONLY

3
V
CONTAINS DEHP

ICU Medical, Inc.,
Lake Forest, Illinois, 60045, USA

IM-4342

icumedical

PRINCIPAL DISPLAY PANEL - 50 mL Bag Pouch Label - WR-0536

TO OPEN – TEAR AT NOTCH
NDC 0990-7077-14
For use only with a calibrated infusion device.
HIGHLY CONCENTRATED

20
mEq

POTASSIUM
CHLORIDE Inj.

400
mEq/L

Total in 50 mL

Each 50 mL contains potassium chloride 1.49 g in water for injection. Electrolytes
per 1000 mL: potassium 400 mEq; chloride 400 mEq.
799 mOsmol/liter (CALC.)
pH 5.8 (4.0 to 8.0)
Hypertonic – may cause vein damage.

DO NOT ADD SUPPLEMENTARY MEDICATION. WHENEVER POSSIBLE USE
CENTRAL ROUTE.

Discontinue infusion if adverse reaction occurs.

Single-dose container. For I.V. use. Usual dosage: See insert. Sterile, nonpyrogenic.
Use only if solution is clear. After removing the overwrap, check for minute leaks by
squeezing container firmly. If leaks are found, discard unit as sterility may be impaired.
Must not be used in series connections.

The overwrap is a moisture barrier. Do not remove unit from overwrap until ready
for use. Use unit promptly when pouch is opened. Store at 20 to 25°C (68 to 77°F).
[See USP Controlled Room Temperature.] Protect from freezing. See insert.

Rx only

7
OTHER

F WR-0536

ICU Medical, Inc., Lake Forest, Illinois, 60045, USA

icumedical